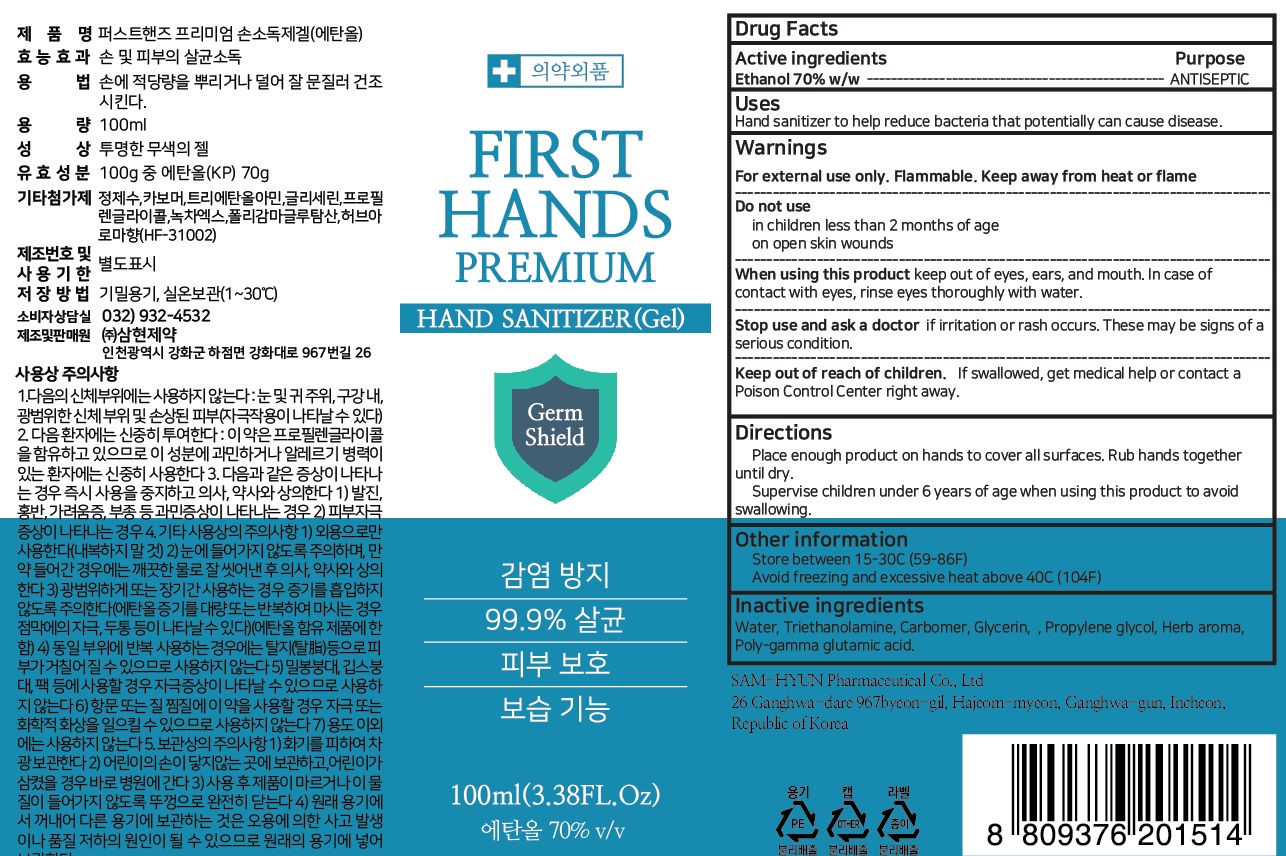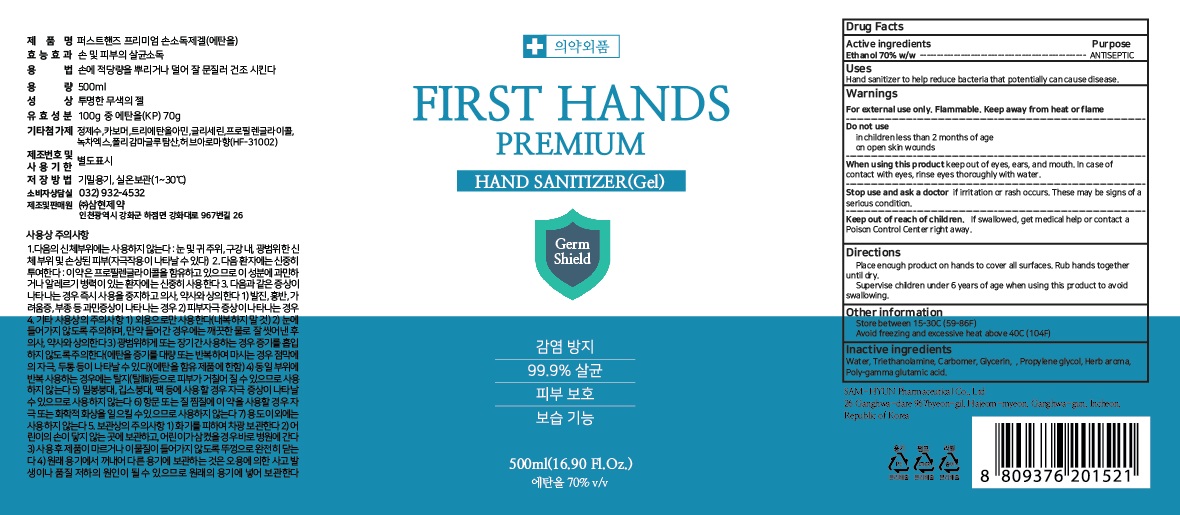 DRUG LABEL: First Hands premium hand sanitizer
NDC: 75765-020 | Form: GEL
Manufacturer: Samhyun pharma
Category: otc | Type: HUMAN OTC DRUG LABEL
Date: 20250318

ACTIVE INGREDIENTS: ALCOHOL 70 mL/100 mL
INACTIVE INGREDIENTS: WATER; TROLAMINE; CARBOMER HOMOPOLYMER, UNSPECIFIED TYPE; GLYCERIN; PROPYLENE GLYCOL

ACTIVE INGREDIENT

Active ingredients: Ethanol 70% w/w

INACTIVE INGREDIENT

Inactive ingredients:

Water, Triethanolamine, Carbomer, Glycerin, Propylene glycol, Herb aroma, Poly-gamma glutamic acid

PURPOSE

Purpose: ANTISEPTIC

WARNINGS

For external use only. Flammable. Keep away from heat or flame
--------------------------------------------------------------------------------------------------------
Do not use
• in children less than 2 months of age
• on open skin wounds
--------------------------------------------------------------------------------------------------------
When using this product keep out of eyes, ears, and mouth. In case of contact with eyes, rinse eyes thoroughly with water.
--------------------------------------------------------------------------------------------------------
Stop use and ask a doctor if irritation or rash occurs. These may be signs of a serious condition.

Keep out of reach of children. If swallowed, get medical help or contact a Poison Control Center right away.

Uses

Hand sanitizer to help reduce bacteria that potentially can cause disease.

Directions

• Place enough product on hands to cover all surfaces. Rub hands together until dry.
• Supervise children under 6 years of age when using this product to avoid swallowing.

Other information

• Store between 15-30C (59-86F)
• Avoid freezing and excessive heat above 40C (104F)